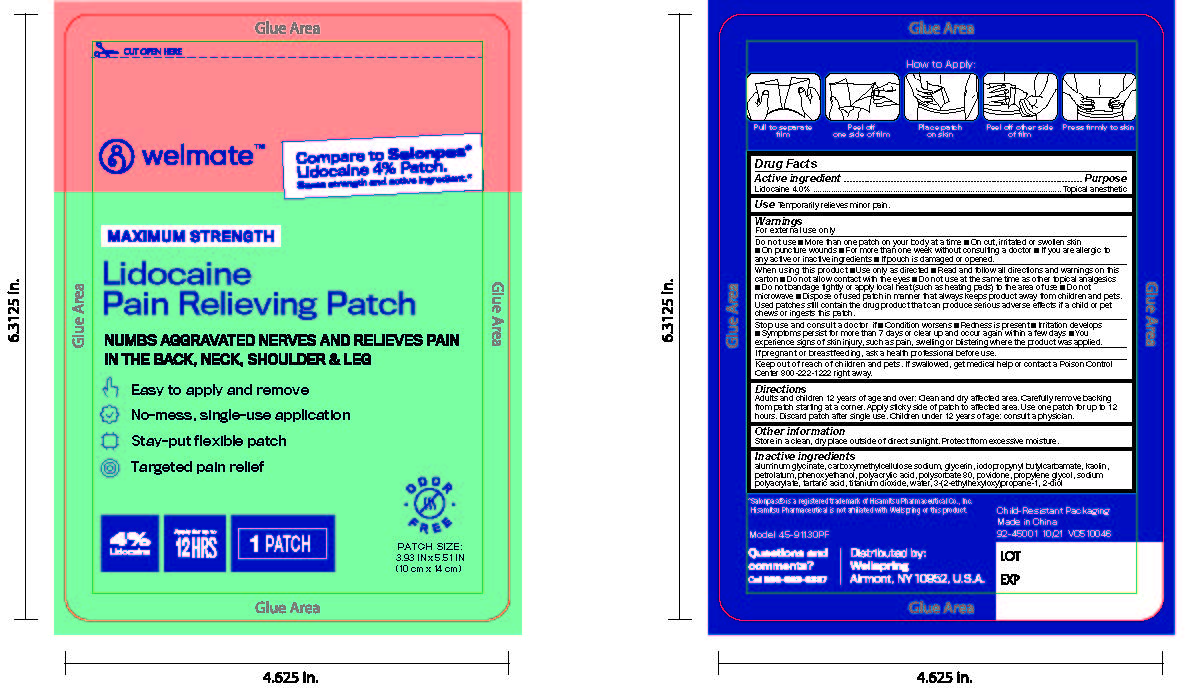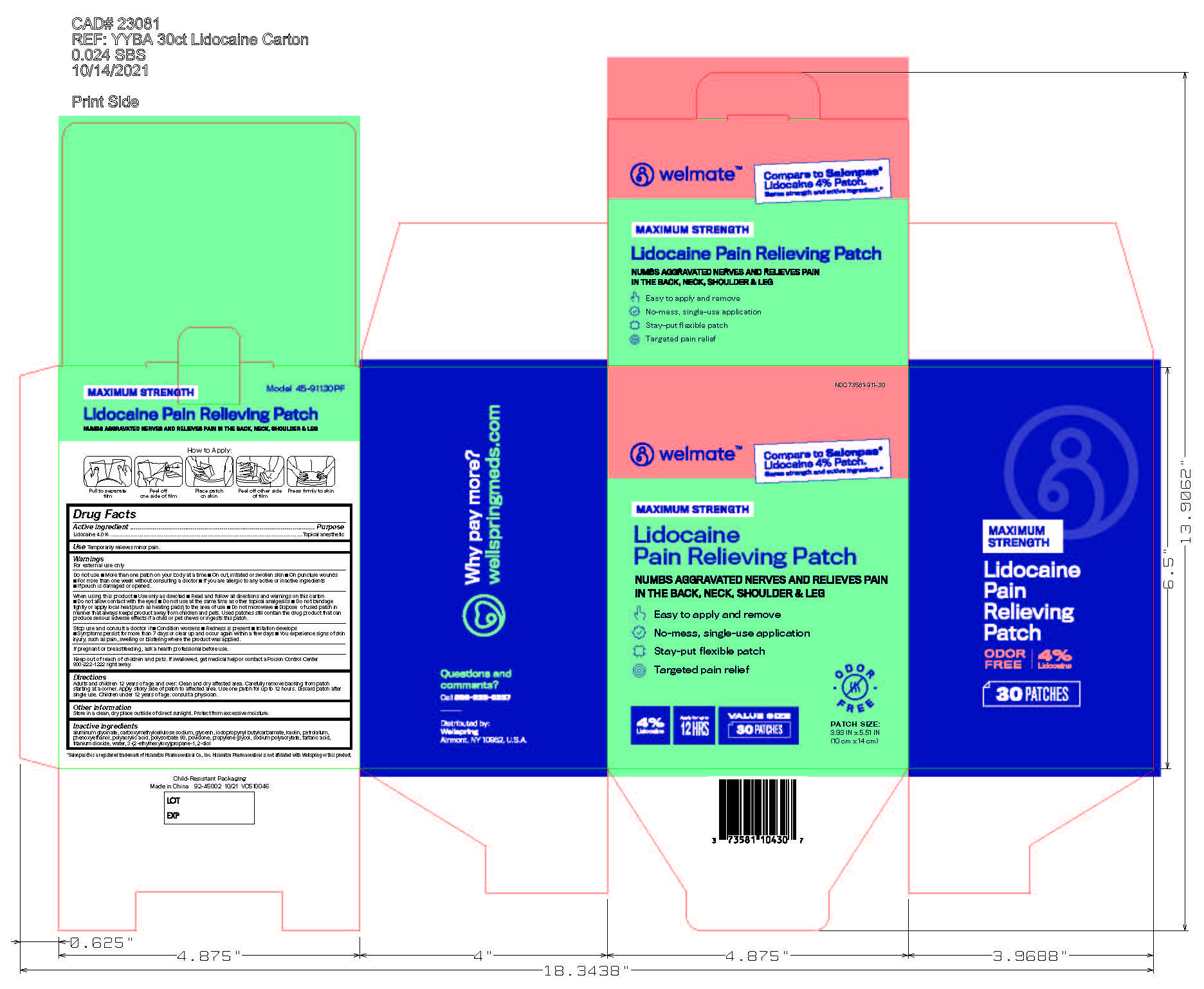 DRUG LABEL: Welmate Lidocaine Pain Relieving Patch
NDC: 73581-911 | Form: PATCH
Manufacturer: Yyba Corporation
Category: otc | Type: HUMAN OTC DRUG LABEL
Date: 20260118

ACTIVE INGREDIENTS: LIDOCAINE 4 g/100 g
INACTIVE INGREDIENTS: POLYACRYLIC ACID (8000 MW); PETROLATUM; CARBOXYMETHYLCELLULOSE SODIUM; IODOPROPYNYL BUTYLCARBAMATE; ETHYLHEXYLGLYCERIN; DIHYDROXYALUMINUM AMINOACETATE; SODIUM POLYACRYLATE (8000 MW); KAOLIN; GLYCERIN; POLYSORBATE 80; PHENOXYETHANOL; PROPYLENE GLYCOL; POVIDONE, UNSPECIFIED; TARTARIC ACID; TITANIUM DIOXIDE; WATER

Welmate Lidocaine Pain Relieving Patch

Active ingredient

Lidocaine 4%

Purpose

Topical anesthetic

Uses

For temporary relieves minor pain

Warnings

For external use only

Do not use

- more than one patch on your body at a time
- On cut, irritated or swollen skin
- On puncture wounds
- For more than one week without consulting a doctor
- If you are allergic to any active or inactive ingredients
- if pouch is damaged or opened.

When using this product

- use only as directed
- read and follow directions and warnings on this carton
- do not allow contact with eyes.
- Do not use at the same time as other topical analgesics
- Do not bandage tightly or apply local heat (such as heating pads) to the area of use
- Do not microwave
- Dispose of used patch in manner that always keeps product away from children and pets. Used patches still contain the drug product that can produce serious adverse effects if a child or pet chews or ingests this patch.

Stop use and ask a doctor if

- conditions worsen
- Redness is present
- irritation develops
- symptoms persist for more than 7 days or clear up and occur again within a few days
- You experience signs of skin injury, such as pain, swelling, or blistering where the product was applied.

If pregnant or breast-feeding,

ask a health professional before use.

Keep out of reach of children and pets

If swallowed, get medical help or contact a Poison Control Center 800-222-1222 right away.

Directions

Adults and children 12 years of age and over:

- clean and dry affected area
- carefully remove backing from patch starting at a corner.
- Apply sticky side of patch to affected area.
- Use one patch for up to 12 hours.
- Discard patch after single use

Children under 12 years of age:consult a physician

Other information

- Store in a clean, dry place outside of direct sunlight
- Protect from excessive moisture

Inactive ingredients

aluminum glycinate, carboxymethylcellulose sodium, glycerin, iodopropynyl butylcarbamate, kaolin, petrolatum, phenoxyethanol, polyacrylic acid, polysorbate80, povidone, propylene glycol, sodium polyacrylate, tartaric acid, titanium dioxide, water, 3-(2-ethylhexyloxy)propane-1,2-diol

Questions or comments?

Toll free 866-933-6337www.salonpas.us